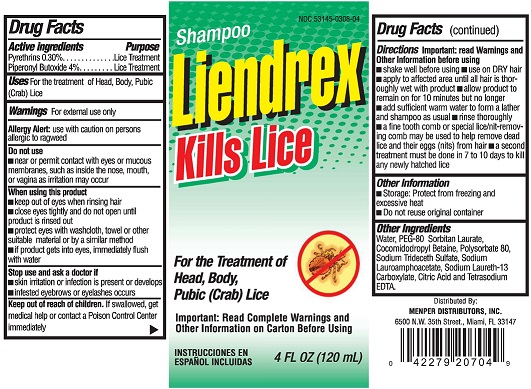 DRUG LABEL: LIENDREX
NDC: 53145-308 | Form: SHAMPOO
Manufacturer: Menper Distributors Inc.
Category: otc | Type: HUMAN OTC DRUG LABEL
Date: 20250722

ACTIVE INGREDIENTS: PIPERONYL BUTOXIDE 4 g/100 mL; PYRETHRUM EXTRACT 0.3 g/100 mL
INACTIVE INGREDIENTS: WATER; PEG-20 SORBITAN ISOSTEARATE; COCAMIDOPROPYL BETAINE; POLYSORBATE 80; SODIUM TRIDECETH SULFATE; SODIUM LAUROAMPHOACETATE; SODIUM LAURETH-13 CARBOXYLATE; ANHYDROUS CITRIC ACID; EDETATE SODIUM

Liendrex

ACTIVE INGREDIENTS

PYRETHINS 0.30%

PIPERONYL BUTOXIDE 4%

PURPOSE

LICE TREATMENT

INDICATIONS AND USAGE

USES: FOR THE TREATMENT OF HEAD, BODY, PUBIC (CRAB) LICE.

WARNINGS

FOR EXTERNAL USE ONLY.

ALLERGY ALERT: USE WITH CAUTION ON PERSONS WITH ALLERGIC TO RAGWEED.

DO NOT USE

- NEAR OR PERMIT CONTACT WITH EYES OR MUCOUS MEMBRANES, SUCH AS INSIDE THE NOSE, MOUTH, OR VAGINA AS IRRITATION MAY OCCURE.

WHEN USING THIS PRODUCT

- KEEP OUT OF EYES WHEN RINSING HAIR.
- CLOSE EYES TIGHTLY AND DO NOT OPEN UNTIL PRODUCT IS RINSED OUT.
- PROTECT EYES WITH WASHCLOTH, TOWEL OR OTHER SUITABLE MATERIAL OR BY SIMILAR METHOD.
- IF PRODUCT GETS INTO EYES, IMMEDIATELY FLUSH WITH WATER.

STOP USE AND ASK A DOCTOR IF

- SKIN IRRITATION OR INFECTION IS PRESENT OR DEVELOPS.
- INFESTED EYEBROWS OR EYELASHES OCCURS.

KEEP OUT OF REACH OF CHILDREN. IF SWALLOWED, GET MEDICAL HELP OR CONTACT A POISON CONTROL CENTER IMMEDIATELY.

DIRECTIONS

IMPORTANT: READ WARNINGS AND OTHER INFORMATION BEFORE USING.

- SHAKE WELL BEFORE USING.
- USE ON DRY HAIR.
- APPLY TO AFFECTED AREA UNTIL ALL HAIR IS THOROUGHLY WET WITH PRODUCT.
- ALLOW PRODUCT TO REMAIN ON FOR 10 MINUTES BUT NO LONGER.
- ADD SUFFICIENT WARM WATER TO FORM A LATHER AND SHAMPOO AS USUAL.
- RINSE THOROUGHLY.
- A FINE TOOTH COMB OR SPECIAL LICE/NIT-REMOVAL COMB MAY BE USED TO HELP REMOVE DEAD LICE AND THEIR EGGS (NITS) FROM HAIR.
- A SECOND TREATMENT MUST BE DONE IN 7 TO 10 DAYS TO KILL ANY NEWLY HATCHED LICE.

OTHER INFORMATION

- STORAGE: PROTECT FROM FREEZING AND EXCESSIVE HEAT.
- DO NOT REUSE ORIGINAL CONTAINER.

INACTIVE INGREDIENT

OTHER INGREDIENTS

WATER, PEG-80 SORBITAN LAURATE, COCAMIDOPROPYL BETAINE, POLYSORBATE 80, SODIUM TRIDECETH SULFATE, SODIUM LAUROAMPHOACETATE, SODIUM LAURETH-13 CARBOXYLATE, CITRIC ACID AND TETRASODIUM EDTA.